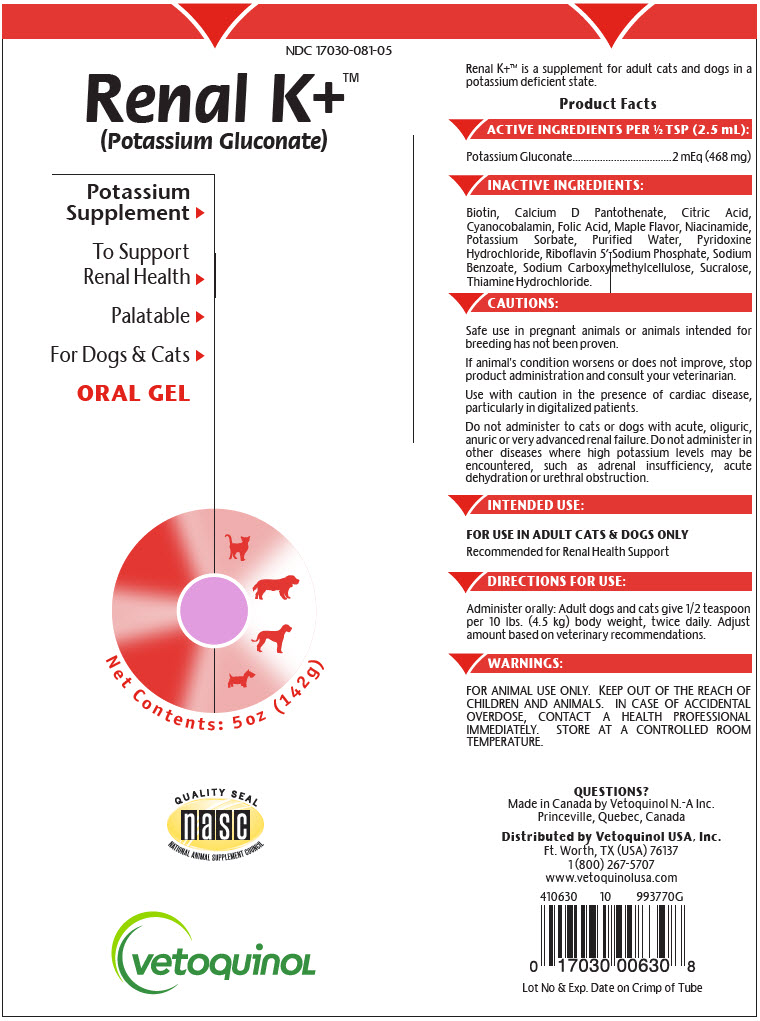 DRUG LABEL: Renal K Plus
NDC: 17030-081 | Form: GEL
Manufacturer: Vetoquinol USA, Inc.
Category: animal | Type: OTC ANIMAL DRUG LABEL
Date: 20200213

ACTIVE INGREDIENTS: Potassium Gluconate 187.2 mg/2.5 g
INACTIVE INGREDIENTS: BIOTIN; CALCIUM PANTOTHENATE; CITRIC ACID MONOHYDRATE; CYANOCOBALAMIN; FOLIC ACID; NIACINAMIDE; POTASSIUM SORBATE; WATER; PYRIDOXINE HYDROCHLORIDE; RIBOFLAVIN 5'-PHOSPHATE SODIUM ANHYDROUS; SODIUM BENZOATE; CARBOXYMETHYLCELLULOSE SODIUM, UNSPECIFIED FORM; SUCRALOSE; THIAMINE HYDROCHLORIDE

Renal K+™

VETERINARY INDICATIONS

Renal K+™ is a supplement for adult cats and dogs in a potassium deficient state.

Product Facts

ACTIVE INGREDIENTS PER ½ TSP (2.5 mL):

Potassium Gluconate | 2 mEq (468 mg)

INACTIVE INGREDIENTS:

Biotin, Calcium D Pantothenate, Citric Acid, Cyanocobalamin, Folic Acid, Maple Flavor, Niacinamide, Potassium Sorbate, Purified Water, Pyridoxine Hydrochloride, Riboflavin 5'-Sodium Phosphate, Sodium Benzoate, Sodium Carboxymethylcellulose, Sucralose, Thiamine Hydrochloride.

CAUTIONS:

Safe use in pregnant animals or animals intended for breeding has not been proven.

If animal's condition worsens or does not improve, stop product administration and consult your veterinarian.

Use with caution in the presence of cardiac disease, particularly in digitalized patients.

Do not administer to cats or dogs with acute, oliguric, anuric or very advanced renal failure. Do not administer in other diseases where high potassium levels may be encountered, such as adrenal insufficiency, acute dehydration or urethral obstruction.

INTENDED USE:

FOR USE IN ADULT CATS & DOGS ONLY

Recommended for Renal Health Support

DIRECTIONS FOR USE:

Administer orally: Adult dogs and cats give 1/2 teaspoon per 10 lbs. (4.5 kg) body weight, twice daily. Adjust amount based on veterinary recommendations.

WARNINGS:

FOR ANIMAL USE ONLY. KEEP OUT OF THE REACH OF CHILDREN AND ANIMALS. IN CASE OF ACCIDENTAL OVERDOSE, CONTACT A HEALTH PROFESSIONAL IMMEDIATELY. STORE AT A CONTROLLED ROOM TEMPERATURE.

QUESTIONS?

Made in Canada by Vetoquinol N.-A Inc.
Princeville, Quebec, Canada

Distributed by Vetoquinol USA, Inc.
Ft. Worth, TX (USA) 76137
1 (800) 267-5707
www.vetoquinolusa.com

Lot No & Exp. Date on Crimp of Tube

PRINCIPAL DISPLAY PANEL - 142 g Tube Label

NDC 17030-081-05

Renal K+™
(Potassium Gluconate)

Potassium
Supplement ▶

To Support
Renal Health ▶

Palatable ▶

For Dogs & Cats ▶

ORAL GEL

Net Contents: 5oz (142g)

QUALITY SEAL
nasc
NATIONAL ANIMAL SUPPLEMENT COUNCIL

vetoquinol